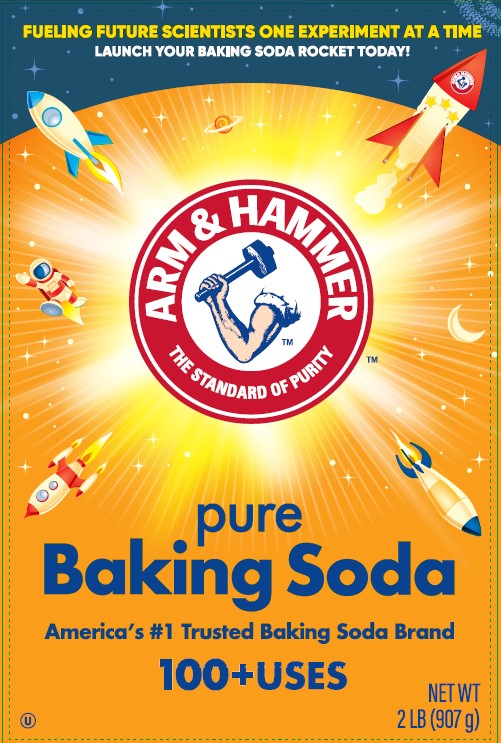 DRUG LABEL: Arm and Hammer Baking Soda
NDC: 10237-591 | Form: POWDER, FOR SOLUTION
Manufacturer: Church & Dwight Co., Inc.
Category: otc | Type: HUMAN OTC DRUG LABEL
Date: 20251211

ACTIVE INGREDIENTS: SODIUM BICARBONATE 1 g/1 g

Arm and Hammer Baking Soda

Drug Facts

Active Ingredient

Sodium Bicarbonate 100%

Purpose

Skin Protectant

Uses

temporarily protects and helps relieve minor skin irritation and itching due to:

- poison ivy, oak, sumac
- insect bites

Warnings

When using this product

- do not get in eyes
- in some cases, soaking too long may overdry skin

Stop use and ask a doctor if

- condition worsens
- symptoms last more than 7 days or clear up and occur again within a few days

Keep out of reach of children. If swallowed, get medical help or contact a Poison Control Center right away

Directions

- adults and children 2 years of age and over:

For use as a paste:

- add enough water to the sodium bicarbonate to form a paste
- apply to the affected area of the skin as needed, or as directed by a doctor
- children under 2 years: ask a doctor

For use as a soak in the bath

- dissolve 1 to 2 cups in a tub of warm water
- soak for 10 to 30 minutes as needed, or as directed by a doctor
- pat dry (do not rub) to keep a thin layer on the skin
- children under 2 years: ask a doctor

For use as a compress or wet dressing

- add sodium bicarbonate to water to make a mixture in a container
- soak a clean, soft cloth in the mixture
- apply cloth loosely to affected area for 15-30 minutes
- repeat as needed or as directed by a doctor
- discard mixture after each use
- children under 2 years: ask a doctor

Purpose

Antacid

Uses

relieves:

- heartburn • sour stomach • acid indigestion • and upset stomach due to these symptoms

Warnings

Do not administer to children under age 5

Ask a doctor before use if you have

- a sodium restricted diet

Ask a doctor or pharmacist before use if you are

- presently taking a prescription drug. Anatacids may interact with certain prescription drugs.

When using this product

- do not take more then the maximum dose in a 24-hour period
- do not use the maximum dosage for more than 2 weeks

Stop use and ask a doctor if

symptoms last more than 2 weeks.

WARNINGS AND PRECAUTIONS

STOMACH WARNING: TO AVOID SERIOUS INJURY, DO NOT TAKE UNTIL POWDER IS COMPLETELY DISSOLVED. IT IS VERY IMPORTANT NOT TO TAKE THIS PRODUCT WHEN OVERLY FULL FROM FOOD OR DRINK. Consult a doctor if severe stomach pain occurs after taking this product.

Directions

- add 1/2 teaspoon to 1/2 glass (4 fl. oz.) of water every 2 hours, or as directed by physician. Dissolve completely in water. Accurately measure 1/2 teaspoon. DO NOT EXCEED RECOMMENDED DOSE. See Warnings.
- do not take more than the following amounts in 24 hours:
- seven 1/2 teaspoons
- three 1/2 teaspoons if you are over 60 years

Other Information

- each 1/2 teaspoon contains: 656mg sodium.

PACKAGE LABEL

ARM & HAMMERTM

THE STANDARD OF PURITY

pure

Baking Soda

America's #1 Trusted Baking Soda Brand

100+ USES

NET WT. 2 LB. (907g)